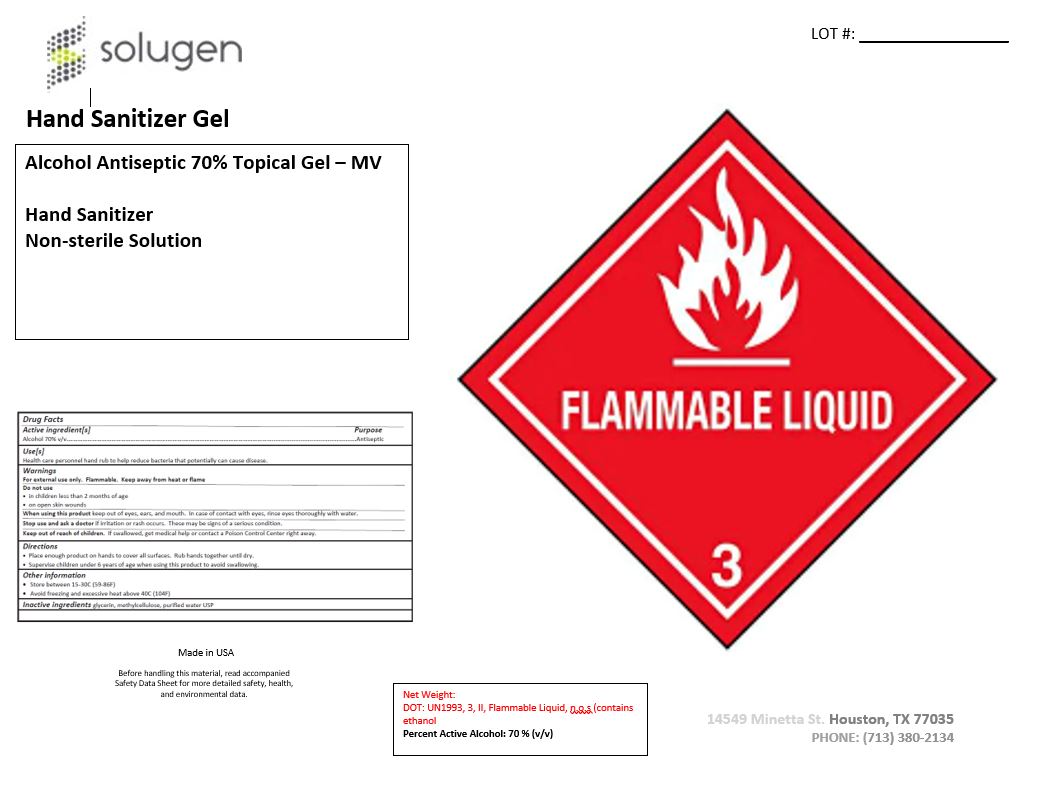 DRUG LABEL: Hand Sanitizer Alcohol Antiseptic 70% Topical Gel -MV
NDC: 71158-005 | Form: GEL
Manufacturer: Solugen, Inc.
Category: otc | Type: HUMAN OTC DRUG LABEL
Date: 20200901

ACTIVE INGREDIENTS: ALCOHOL 70 mL/100 mL
INACTIVE INGREDIENTS: GLYCERIN 1.25 mL/100 mL; WATER; HYDROXYMETHYL CELLULOSE 1.05 mL/100 mL

Hand Sanitizer Alcohol Antiseptic 70% Topical Gel - MV

This is a hand sanitizer manufactured according to the part333A of the OTC monograph.
The hand sanitizer is manufactured using only the following United States Pharmacopoeia (USP) grade ingredients in the preparation of the product (percentag
formulation)
a. Alcohol (ethanol) (USP or Food Chemical Codex (FCC) grade) (70%, volume/volume (v/v) in an aqueos solution denatured according to Alcohol and Tobacco
Bureau regulations in 27 CFR part 20.
b. Glycerol (1.25% v/v).
c. Hydroxymethyl Cellulose (1.05% v/v) .
d. Sterile distilled water or boiled cold water.

Active Ingredient(s)

Alcohol 70% v/v. Purpose: Antiseptic

Purpose

Antiseptic, Hand Sanitizer

Use

Hand Sanitizer to help reduce bacteria that potentially can cause disease. For use when soap and water are not available.

Warnings

For external use only. Flammable. Keep away from heat or flame

Do not use

- in children less than 2 months of age
- on open skin wounds

When using this product keep out of eyes, ears, and mouth. In case of contact with eyes, rinse eyes thoroughly with water.
Stop use and ask a doctor if irritation or rash occurs. These may be signs of a serious condition.
Keep out of reach of children. If swallowed, get medical help or contact a Poison Control Center right away.

Stop use and ask a doctor if irritation or rash occurs. These may be signs of a serious condition.

Keep out of reach of children. If swallowed, get medical help or contact a Poison Control Center right away.

Directions

- Place enough product on hands to cover all surfaces. Rub hands together until dry.
- Supervise children under 6 years of age when using this product to avoid swallowing.

Other information

- Store between 15-30C (59-86F)
- Avoid freezing and excessive heat above 40C (104F)

Inactive ingredients

glycerin, methylcellulose, purified water USP

Hand Sanitizer Alcohol Antiseptic 70% Topical Gel - MV

18927000 mL NDC: 71158-005-01